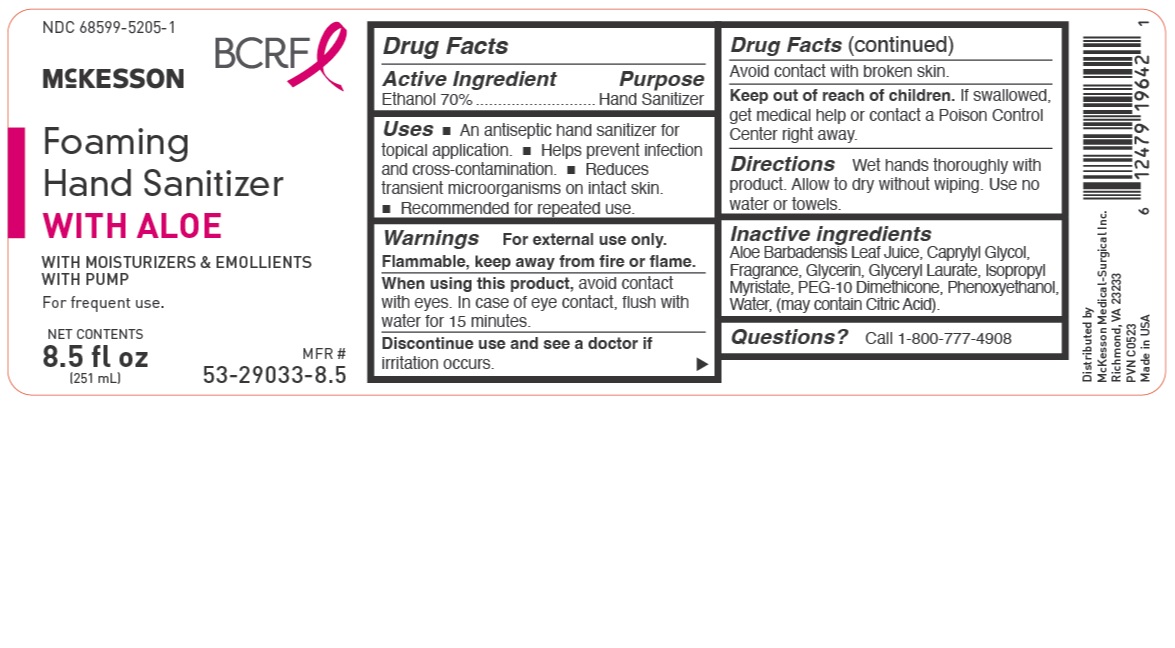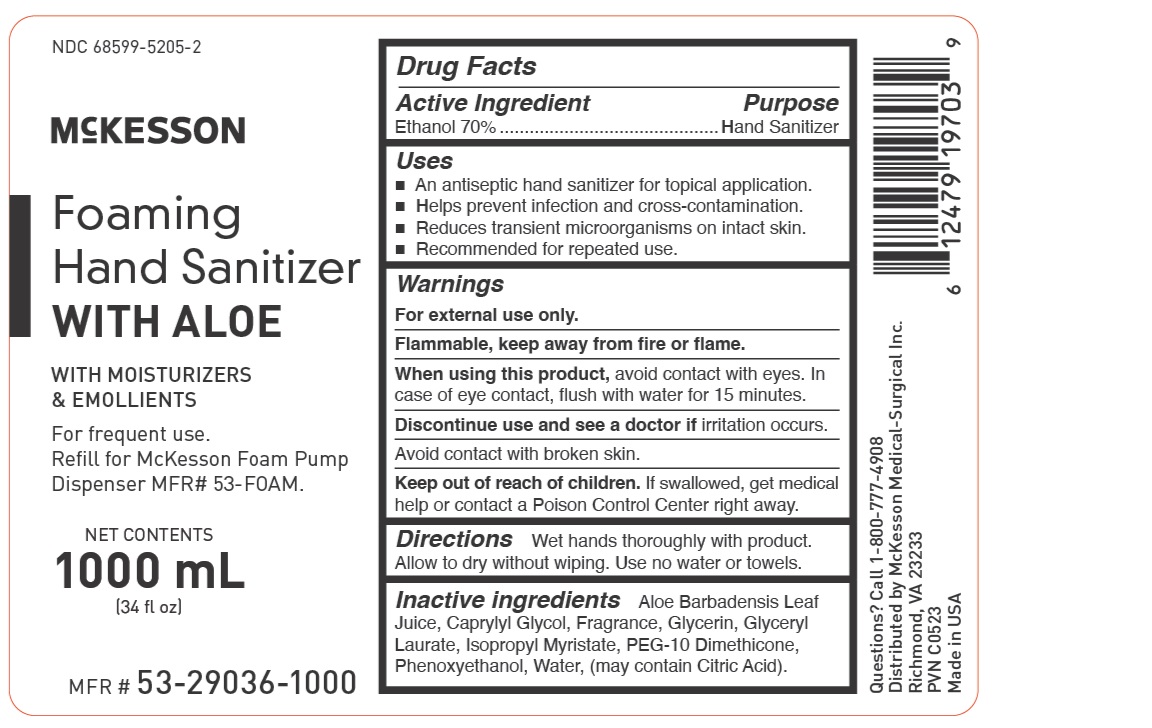 DRUG LABEL: Foaming Instant Hand Sanitizer with Aloe
NDC: 68599-5205 | Form: GEL
Manufacturer: MCKESSON MEDICAL-SURGICAL INC.
Category: otc | Type: HUMAN OTC DRUG LABEL
Date: 20230605

ACTIVE INGREDIENTS: ALCOHOL 70 g/100 g
INACTIVE INGREDIENTS: WATER; ALOE VERA LEAF; CITRIC ACID MONOHYDRATE; ISOPROPYL MYRISTATE; GLYCERYL LAURATE; CAPRYLYL GLYCOL; PEG-10 DIMETHICONE (600 CST); PHENOXYETHANOL

Active Ingredient Purpose

Ethanol 70% .................................................... hand sanitizer

Uses

- an antiseptic hand sanitizer for topical application.
- helps prevent infection and cross-contamination.
- reduces transient microorganisms on intact skin.
- recommended for repeated use.

Keep out of reach of children. If swallowed, get medical help or contact a Poison Control Center right away.

INDICATIONS AND USAGE

McKesson Foaming Hand Sanitizer with Aloe

With Moisturizers & Emollients

With Pump

for frequent use.

Directions

Wet hands thoroughly with product. Allow to dry without wiping. Use no water or towels.

Warnings

For external use only.

Flammable, keep away from fire or flame.

When using this product avoid contact with eyes. In case of eye contact, flush with water for 15 minutes.

Discontinue use and see a doctor if irritation occurs.

Avoid contact with broken skin.

Inactive Ingredients

Aloe Barbadensis Leaf Juice, Caprylyl Glycol, Fragrance, Glycerin, Glyceryl
Laurate, Isopropyl Myristate, PEG-10 Dimethicone, Phenoxyethanol, Water, (may contain Citric Acid).